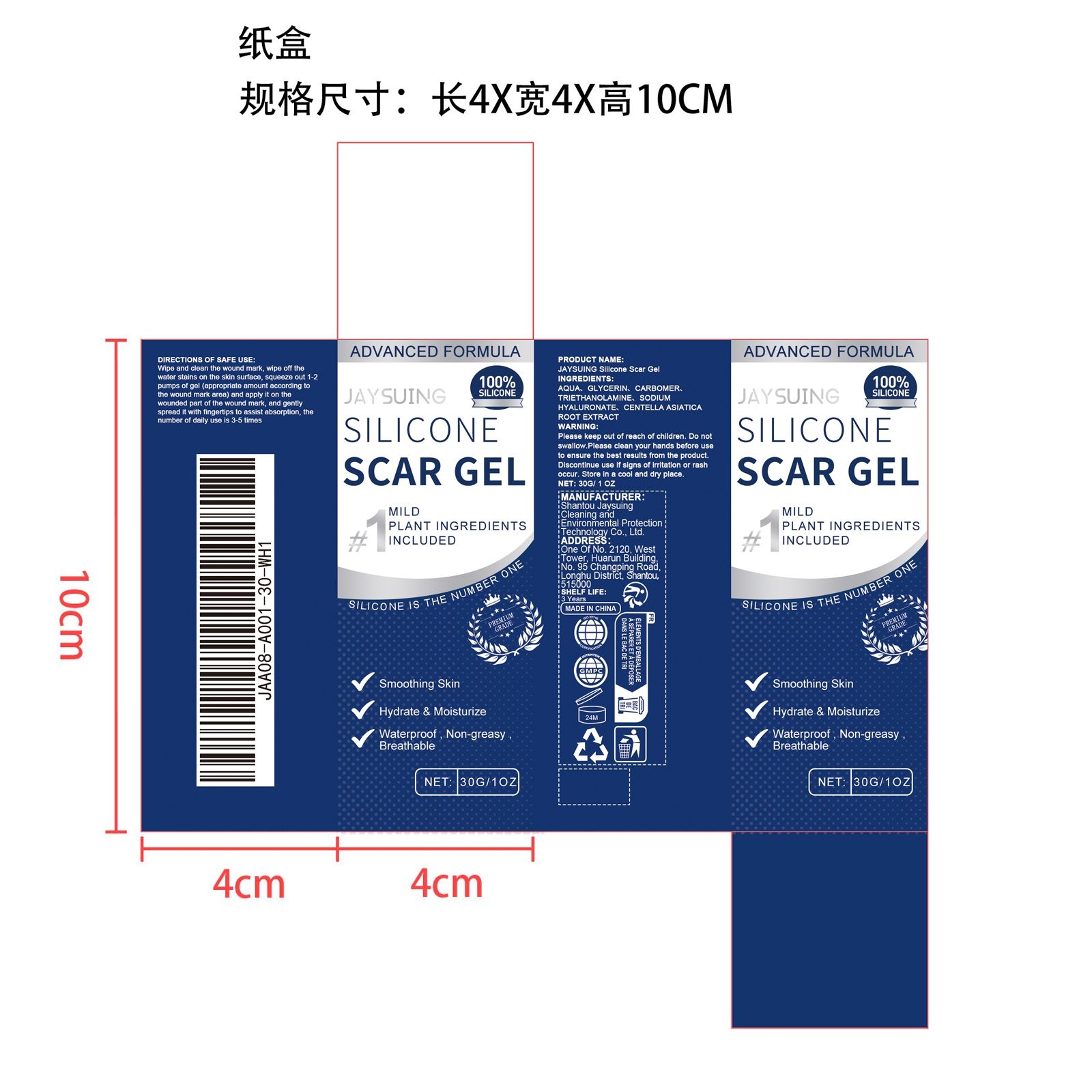 DRUG LABEL: JAYSUING Silicone Scar Gel
NDC: 85060-007 | Form: GEL
Manufacturer: Shantou Jaysuing Cleaning and Environmental Protection Technology Co., Ltd.
Category: otc | Type: HUMAN OTC DRUG LABEL
Date: 20251127

ACTIVE INGREDIENTS: CENTELLA ASIATICA ROOT 0.006 mg/30 mg
INACTIVE INGREDIENTS: SODIUM HYALURONATE 0.03 mg/30 mg; TRIETHANOLAMINE 0.06 mg/30 mg; CARBOMER 0.06 mg/30 mg; AQUA 27.444 mg/30 mg; GLYCERIN 2.4 mg/30 mg

ACTIVE INGREDIENT

CENTELLA ASIATICA ROOT EXTRACT

PURPOSE

Smoothing Skin.

Hydrate & Moisturize.

Waterproof, Non-greasy Breathable.

WHEN USING

Wipe and clean the wound mark, wipe off the water stains on the skin surface, squeeze out 1-2 pumps of gel (appropriate amount according to the wound mark area) and apply it on the wounded part of the wound mark, and gently spread it with fingertips to assist absorption, the number of daily use is 3-5 times.

WARNINGS

Please keep out of reach of children. Do not swallow.Please clean your hands before use to ensure the best results from the product. Discontinue use if signs of irritation or rash occur. Store in a cool and dry place.

DO NOT USE

Discontinue use if signs of irritation or rash occur.

STOP USE

Discontinue use if signs of irritation or rash occur.

KEEP OUT OF REACH OF CHILDREN

Please keep out of reach of children. Do not swallow.Please clean your hands before use to ensure the best results from the product. Discontinue use if signs of irritation or rash occur. Store in a cool and dry place.

STORAGE AND HANDLING

Store in a cool and dry place.

INACTIVE INGREDIENT

AQUA、GLYCERIN、CARBOMER、TRIETHANOLAMINE、SODIUM HYALURONATE

INDICATIONS AND USAGE

Wipe and clean the wound mark, wipe off the water stains on the skin surface, squeeze out 1-2 pumps of gel (appropriate amount according to the wound mark area) and apply it on the wounded part of the wound mark, and gently spread it with fingertips to assist absorption, the number of daily use is 3-5 times.

DOSAGE AND ADMINISTRATION

Wipe and clean the wound mark, wipe off the water stains on the skin surface, squeeze out 1-2 pumps of gel (appropriate amount according to the wound mark area) and apply it on the wounded part of the wound mark, and gently spread it with fingertips to assist absorption, the number of daily use is 3-5 times.